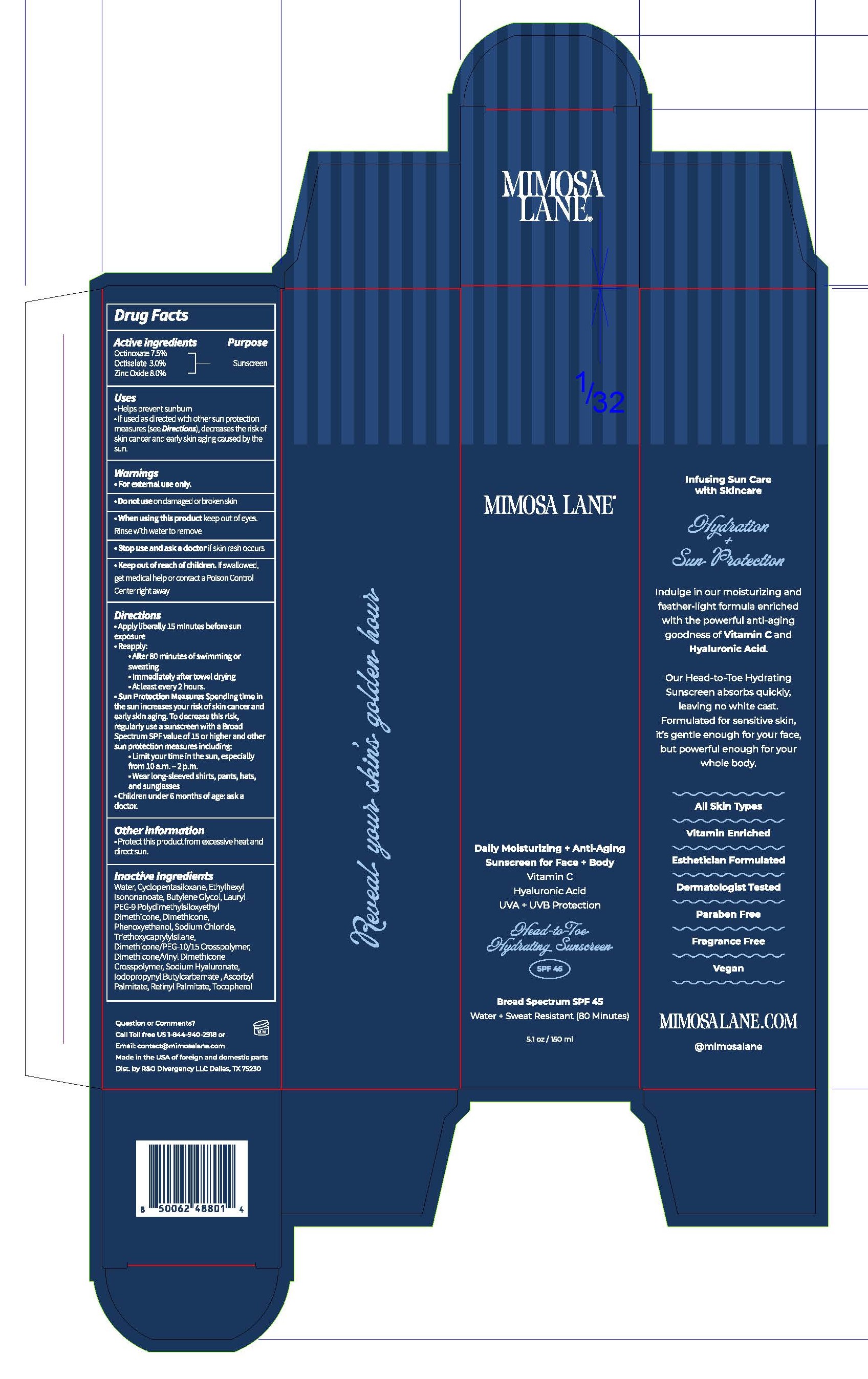 DRUG LABEL: Mimosa Lane SPF45
NDC: 84554-0006 | Form: CREAM
Manufacturer: R&G Divergency LLC
Category: otc | Type: HUMAN OTC DRUG LABEL
Date: 20260124

ACTIVE INGREDIENTS: OCTINOXATE 75 g/1000 g; OCTISALATE 30 g/1000 g; ZINC OXIDE 80 g/1000 g
INACTIVE INGREDIENTS: TRIETHOXYCAPRYLYLSILANE; BUTYLENE GLYCOL; PHENOXYETHANOL; IODOPROPYNYL BUTYLCARBAMATE; WATER; SODIUM CHLORIDE; HYALURONIC ACID; CYCLOMETHICONE; ASCORBYL PALMITATE; VITAMIN A PALMITATE; DIMETHICONE/PEG-10/15 CROSSPOLYMER; DIMETHICONE/VINYL DIMETHICONE CROSSPOLYMER (SOFT PARTICLE); LAURYL PEG-9 POLYDIMETHYLSILOXYETHYL DIMETHICONE; ETHYLHEXYL ISONONANOATE; TOCOPHEROL

Mimosa Lane SPF45

Warnings

For external use only. Do not use on damaged or broken skin. When using this product keep out of eyes. Rinse with water to remove. Stop use and ask a physician if rash occurs. If product is swallowed get medical help or contact a Poison Control Center right away.

Active Ingredients

Octinoxate 7.5%
Octisalate 3.0%
Zinc Oxide 8.0%

Indications and Usage

Helps prevent sunburn. If used as directed with other sun protection measure (See Directions), decreases the risk of skin cancer and early skin aging caused by the sun.

Purpose

Sunscreen

Keep out of reach of children

Directions

Apply liberally 15 minutes before sun exposure. Reapply: after 80 minutes of swimming or sweating, immediately after towel drying and at least every 2 hours. Sun Protection Measures: Spending time in the sun increases your risk of skin cancer and early skin aging. To decrease this risk, regularly use a sunscreen with a broad-spectrum SPF of 15 or higher and other sun protection measures including: limit time in the sun, especially from 10 am to 2 pm. Wear long-sleeve shirts, pants, hats, and sunglasses. Children under 6 months: ask a physician.

Other information

Protect this product from excessive heat and direct sun.

Inactive Ingredients

water, cyclopentasiloxane, ethylhexyl isononanoate, butylene glycol, lauryl PEG-9 polydimethylsiloxyethyl dimethicone, dimethicone, phenoxyethanol, sodium chloride, triethoxycaprylylsilane, dimethicone/PEF-10/15 crosspolymer, dimethicone/vinyl dimethicone crosspolymer, sodium hyaluronate, iodopropynyl butylcarbamate, ascorbyl palmitate, retinyl palmitate, tocopherol

Questions

Call toll free 1-844-940-2918
Email: contact@mimosalane.com